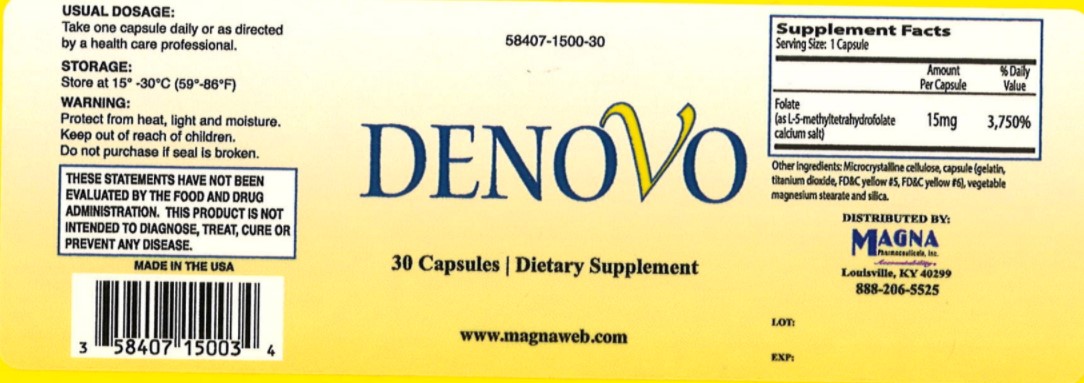 DRUG LABEL: Denovo
NDC: 58407-150 | Form: CAPSULE
Manufacturer: Magna Pharmaceuticals, Inc.
Category: other | Type: Dietary Supplement
Date: 20200922

ACTIVE INGREDIENTS: LEVOMEFOLATE CALCIUM 15 mg/1 1
INACTIVE INGREDIENTS: GELATIN; WATER; MICROCRYSTALLINE CELLULOSE; TITANIUM DIOXIDE; MAGNESIUM STEARATE; FD&C YELLOW NO. 5; FD&C YELLOW NO. 6

Denovo

Supplement Facts

Serving Size: 1 capsule

Servings per Container: 30

Each capsule contains the following:

Folate [as 15,000mcg (as 15mg) DFE (dietary folate equivalents) L-5 MTHF (from L-5 methyltetrahydrofolate calcium salt)]

Other Ingredients: Microcrystalline cellulose, capsule (gelatin,titanium dioxide, FD&C yellow #5, FD&C yellow #6), vegetable magnesium stearate, and silica

Warning and Precautions

Folic Acid, when administered in daily doses above 0.1mg may obscure the detection of B12 deficiency (specifically, the administration of folic acid may reverse the hematological manifestations of B12 deficiency, including pernicious anemia, while not addressing the neurological manifestations). 5-MTHF may be less likely than foli acid to mask vitamin B12 deficiency. Folate therapy alone is inadequate for the treatment of a B12 deficiency.

A major depressive episode may be the inital presentation of bipolar disorder. It is generally believed, although not established in controlled trials, that treating such an episode with an antidepressant alone may increase the likelihood of a precipitation of mixed/manic episode in patients at risk for bipolar disorder. Denovo is not an antidepressant. However, 5-MTHF has been shown to enhance antidepressant effects of known antidepressants. Caution is recommended in patients with a history of bipolar illness. Patients with depressive symptoms should be adequately screened to determine if they are at risk for bipolar disorder since mood elevation in this population is possible.

Denovo should always be used under medical supervision.

Safe Handling

Before using this product, tell your doctor or pharmacist of all of the products you use. Keep a list of all our medications with you and share the list with your doctor and pharmacist. No decrease in effectiveness of drugs has been reported witht the use of Denovo.

Allergic reactions have not been reported following the use of oral (6S) -5-methyltetrahydrofolic acid, glucosamine salt.

Take One capsule daily as directed by a health care professional

Store at 15o-30°C (59°-86° F)

Protect from heat, light and moisture. Keep out of reach of children. Do not purchase if seal is broken.

Indication and Use

Adjunctive use in mood disorders

Denovo is indicated for the distinct nutritional requirements for people who have suboptimal levels of L-methylfolate in cerebrospinal fluid, plasma, and/or red blood cells and have major depressive disorder (MDD), with particular emphasis as adjunctive support for individuals who are on antidepressant. Denovo is indicated regardless of MTHFR C6771 polymorphism genotype.

Principal Display Panel- Denovo

Denovo

Dietary Supplement